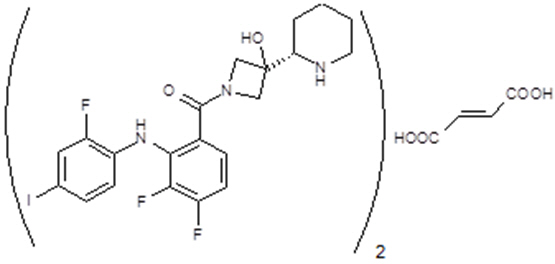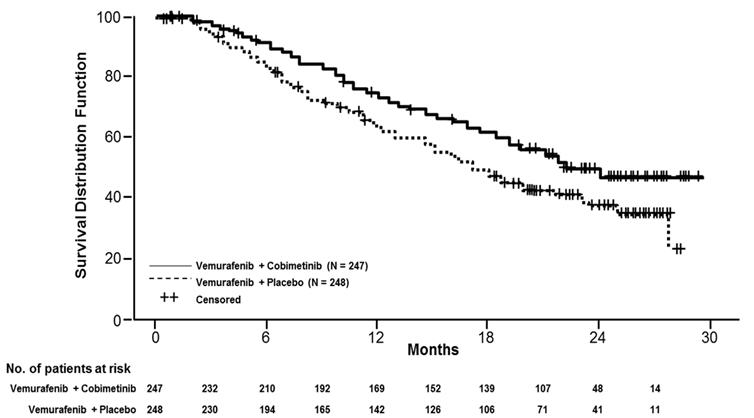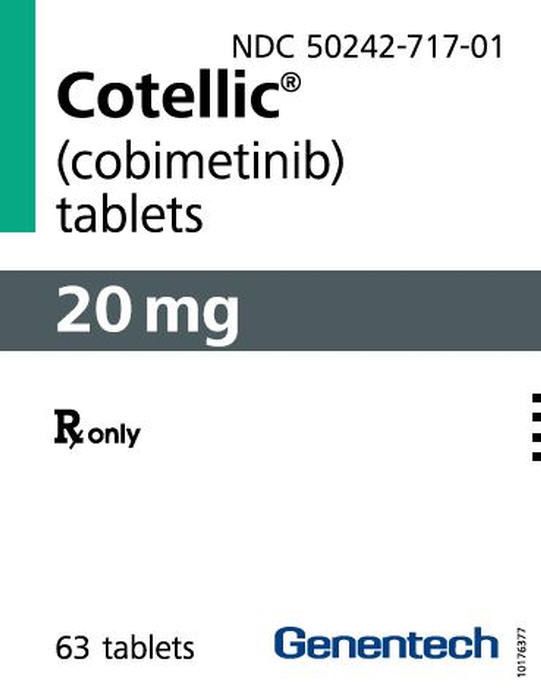 DRUG LABEL: Cotellic
NDC: 50242-717 | Form: TABLET, FILM COATED
Manufacturer: Genentech, Inc.
Category: prescription | Type: HUMAN PRESCRIPTION DRUG LABEL
Date: 20251121

ACTIVE INGREDIENTS: COBIMETINIB FUMARATE 20 mg/1 1
INACTIVE INGREDIENTS: MICROCRYSTALLINE CELLULOSE; LACTOSE MONOHYDRATE; CROSCARMELLOSE SODIUM; MAGNESIUM STEARATE; POLYVINYL ALCOHOL, UNSPECIFIED; TITANIUM DIOXIDE; POLYETHYLENE GLYCOL 3350; TALC

HIGHLIGHTS OF PRESCRIBING INFORMATION

These highlights do not include all the information needed to use COTELLIC safely and effectively. See full prescribing information for COTELLIC.
COTELLIC® (cobimetinib) tablets, for oral use
Initial U.S. Approval: 2015

RECENT MAJOR CHANGES

Indications and Usage, Histiocytic Neoplasms (1.2) | 10/2022
Dosage and Administration (2.1, 2.2) | 10/2022
Warning and Precautions (5.2, 5.3, 5.4, 5.5, 5.6, 5.7) | 10/2022

1 INDICATIONS AND USAGE

COTELLIC® is a kinase inhibitor indicated:

- For the treatment of adult patients with unresectable or metastatic melanoma with a BRAF V600E or V600K mutation, in combination with vemurafenib. (1.1, 14.1)
- As a single agent for the treatment of adult patients with histiocytic neoplasms. (1.2, 14.2)

2 DOSAGE AND ADMINISTRATION

- Confirm the presence of BRAF V600E or V600K mutation in tumor specimens prior to initiation of COTELLIC with vemurafenib for patients with melanoma. (2.1)
- The recommended dose is 60 mg orally once daily for the first 21 days of each 28-day cycle until disease progression or unacceptable toxicity. Take COTELLIC with or without food. (2.2)

3 DOSAGE FORMS AND STRENGTHS

Tablets: 20 mg (3)

4 CONTRAINDICATIONS

None. (4)

5 WARNINGS AND PRECAUTIONS

- New primary malignancies, cutaneous and non-cutaneous: Monitor patients for new malignancies prior to initiation of therapy, while on therapy, and for up to 6 months following the last dose of COTELLIC. (5.1)
- Hemorrhage: Major hemorrhagic events can occur with COTELLIC. Monitor for signs and symptoms of bleeding. (5.2, 2.3)
- Cardiomyopathy: The risk of cardiomyopathy is increased in patients receiving COTELLIC with vemurafenib compared with vemurafenib as a single agent. The safety of COTELLIC has not been established in patients with decreased left ventricular ejection fraction (LVEF). Evaluate LVEF before treatment, after one month of treatment, then every 3 months thereafter during treatment with COTELLIC. (5.3, 2.3)
- Severe Dermatologic Reactions: Monitor for severe skin rashes. Interrupt, reduce, or discontinue COTELLIC. (5.4, 2.3)
- Serous Retinopathy and Retinal Vein Occlusion: Perform an ophthalmological evaluation at regular intervals and for any visual disturbances. Permanently discontinue COTELLIC for retinal vein occlusion (RVO). (5.5, 2.3)
- Hepatotoxicity: Monitor liver laboratory tests during treatment and as clinically indicated. (5.6, 2.3)
- Rhabdomyolysis: Monitor creatine phosphokinase periodically and as clinically indicated for signs and symptoms of rhabdomyolysis. (5.7, 2.3)
- Severe Photosensitivity: Advise patients to avoid sun exposure. (5.8, 2.3)
- Embryo-Fetal Toxicity: Can cause fetal harm. Advise females of reproductive potential of the potential risk to a fetus and to use effective contraception. (5.9, 8.1, 8.3)

6 ADVERSE REACTIONS

Unresectable or Metastatic Melanoma: Most common adverse reactions for COTELLIC (≥20%) are diarrhea, photosensitivity reaction, nausea, pyrexia, and vomiting. The most common (≥5%) Grade 3-4 laboratory abnormalities are increased GGT, increased CPK, hypophosphatemia, increased ALT, lymphopenia, increased AST, increased alkaline phosphatase, hyponatremia. (6.1)

Histiocytic neoplasms: Most common adverse reactions (≥20%) are acneiform dermatitis, diarrhea, infection, fatigue, nausea, edema, dry skin, maculopapular rash, pruritus, dyspepsia, vomiting, dyspnea and urinary tract infections. The most common (≥5%) grade 3-4 lab abnormalities include: Hyponatremia, increased blood creatine phosphokinase, hypokalemia, increased blood creatinine, increased AST, hypocalcemia, lymphopenia, leukopenia, anemia (6.1)

To report SUSPECTED ADVERSE REACTIONS, contact Genentech at 1-888-835-2555 or FDA at 1-800-FDA-1088 or www.fda.gov/medwatch.

7 DRUG INTERACTIONS

Avoid concomitant administration of COTELLIC with strong or moderate CYP3A inducers or inhibitors. (2.3, 7.1, 7.2)

8 USE IN SPECIFIC POPULATIONS

Lactation: Do not breastfeed while taking COTELLIC. (8.2)

FULL PRESCRIBING INFORMATION

1 INDICATIONS AND USAGE

1.1 Unresectable or Metastatic Melanoma

COTELLIC® is indicated for the treatment of adult patients with unresectable or metastatic melanoma with a BRAF V600E or V600K mutation, in combination with vemurafenib.

1.2 Histiocytic Neoplasms

COTELLIC®, as a single agent, is indicated for the treatment of adult patients with histiocytic neoplasms.

2 DOSAGE AND ADMINISTRATION

2.1 Patient Selection for Treatment of Melanoma

Confirm the presence of BRAF V600E or V600K mutation in tumor specimens prior to initiation of treatment with COTELLIC with vemurafenib. Information on FDA-approved tests for the detection of BRAF V600 mutations in melanoma is available at: http://www.fda.gov/CompanionDiagnostics.

2.2 Recommended Dosage

The recommended dosage regimen of COTELLIC is 60 mg (three 20 mg tablets) orally taken once daily for the first 21 days of each 28-day cycle until disease progression or unacceptable toxicity [see Clinical Studies (14)].

Take COTELLIC with or without food [see Clinical Pharmacology (12.3)].

If a dose of COTELLIC is missed or if vomiting occurs when the dose is taken, resume dosing with the next scheduled dose.

2.3 Dose Modifications

Concurrent CYP3A Inhibitors

Do not take strong or moderate CYP3A inhibitors while taking COTELLIC.

If concurrent short term (14 days or less) use of moderate CYP3A inhibitors is unavoidable for patients who are taking COTELLIC 60 mg, reduce COTELLIC dose to 20 mg. After discontinuation of a moderate CYP3A inhibitor, resume previous dose of COTELLIC 60 mg [see Drug Interactions (7.1) and Clinical Pharmacology (12.3)].

Use an alternative to a strong or moderate CYP3A inhibitor in patients who are taking a reduced dose of COTELLIC (40 or 20 mg daily) [see Drug Interactions (7.1) and Clinical Pharmacology (12.3)].

Adverse Reactions

Review the Full Prescribing Information for vemurafenib for recommended dose modifications.

Table 1. Recommended Dose Reductions for COTELLIC
First Dose Reduction | 40 mg orally once daily
Second Dose Reduction | 20 mg orally once daily
Subsequent Modification | Permanently discontinue COTELLIC if unable to tolerate 20 mg orally once daily

Table 2. Recommended Dose Modifications for COTELLIC for Adverse Reactions
Severity of Adverse Reaction [National Cancer Institute Common Terminology Criteria for Adverse Events version 4.0 (NCI CTCAE v4.0)] | Dose Modification for COTELLIC
New Primary Malignancies (cutaneous and non-cutaneous) | No dose modification is required.
Hemorrhage
Grade 3 | Withhold COTELLIC for up to 4 weeks.; - If improved to Grade 0 or 1, resume at the next lower dose level. - If not improved within 4 weeks, permanently discontinue.
Grade 4 | Permanently discontinue.
Cardiomyopathy
Asymptomatic, absolute decrease in LVEF from baseline of greater than 10% and less than institutional lower limit of normal (LLN) | Withhold COTELLIC for 2 weeks; repeat LVEF. Resume at next lower dose if all of the following are present:; - LVEF is at or above LLN and - Absolute decrease from baseline LVEF is 10% or less.; Permanently discontinue if any of the following are present:; - LVEF is less than LLN or - Absolute decrease from baseline LVEF is more than 10%.
Symptomatic LVEF decrease from baseline | Withhold COTELLIC for up to 4 weeks, repeat LVEF. Resume at next lower dose if all of the following are present:; - Symptoms resolve and - LVEF is at or above LLN and - Absolute decrease from baseline LVEF is 10% or less.; Permanently discontinue if any of the following are present:; - Symptoms persist, or - LVEF is less than LLN, or - Absolute decrease from baseline LVEF is more than 10%.
Dermatologic Reactions
Grade 2 (intolerable), Grade 3 or 4 | Withhold or reduce dose.
Serous Retinopathy or Retinal Vein Occlusion
Serous retinopathy | Withhold COTELLIC for up to 4 weeks.; - If signs and symptoms improve, resume at the next lower dose level. - If not improved or symptoms recur at the lower dose within 4 weeks, permanently discontinue.
Retinal vein occlusion | Permanently discontinue COTELLIC.
Liver Laboratory Abnormalities and Hepatotoxicity
First occurrence Grade 4 | Withhold COTELLIC for up to 4 weeks.; - If improved to Grade 0 or 1, then resume at the next lower dose level. - If not improved to Grade 0 or 1 within 4 weeks, permanently discontinue.
Recurrent Grade 4 | Permanently discontinue COTELLIC.
Rhabdomyolysis and Creatine Phosphokinase (CPK) elevations
- Grade 4 CPK elevation - Any CPK elevation and myalgia | Withhold COTELLIC for up to 4 weeks.; - If improved to Grade 3 or lower, resume at the next lower dose level. - If not improved within 4 weeks, permanently discontinue.
Photosensitivity
Grade 2 (intolerable), Grade 3 or Grade 4 | Withhold COTELLIC for up to 4 weeks.; - If improved to Grade 0 or 1, resume at the next lower dose level. - If not improved within 4 weeks, permanently discontinue.
Other
- Grade 2 (intolerable) adverse reactions - Any Grade 3 adverse reactions | Withhold COTELLIC for up to 4 weeks.; - If improved to Grade 0 or 1, resume at the next lower dose level. - If not improved within 4 weeks, permanently discontinue.
First occurrence of any Grade 4 adverse reaction | - Withhold COTELLIC until adverse reaction improves to Grade 0 or 1. Then resume at the next lower dose level, OR - Permanently discontinue.
Recurrent Grade 4 adverse reaction | Permanently discontinue COTELLIC.

3 DOSAGE FORMS AND STRENGTHS

Tablets: 20 mg, white, round, film-coated, debossed on one side with "COB".

4 CONTRAINDICATIONS

None.

5 WARNINGS AND PRECAUTIONS

Review the Full Prescribing Information for vemurafenib for information on the serious risks of vemurafenib.

5.1 New Primary Malignancies

New primary malignancies, cutaneous and non-cutaneous, can occur with COTELLIC.

Cutaneous Malignancies:

In Trial 1, the following cutaneous malignancies or premalignant conditions occurred in the COTELLIC with vemurafenib arm and the vemurafenib arm, respectively: cutaneous squamous cell carcinoma (cuSCC) or keratoacanthoma (KA) (6% and 20%), basal cell carcinoma (4.5% and 2.4%), and second primary melanoma (0.8% and 2.4%). Among patients receiving COTELLIC with vemurafenib, the median time to detection of first cuSCC/KA was 4 months (range: 2 to 11 months), and the median time to detection of basal cell carcinoma was 4 months (range: 27 days to 13 months). The time to onset in the two patients with second primary melanoma was 9 months and 12 months.

Perform dermatologic evaluations prior to initiation of therapy and every 2 months while on therapy. Manage suspicious skin lesions with excision and dermatopathologic evaluation. No dose modifications are recommended for COTELLIC [see Dosage and Administration (2.3)]. Conduct dermatologic monitoring for 6 months following discontinuation of COTELLIC when administered with vemurafenib.

Non-Cutaneous Malignancies:

Based on its mechanism of action, vemurafenib may promote growth and development of malignancies [refer to the Full Prescribing Information for vemurafenib]. In Trial 1, 0.8% of patients in the COTELLIC with vemurafenib arm and 1.2% of patients in the vemurafenib arm developed non-cutaneous malignancies.

Monitor patients receiving COTELLIC, when administered with vemurafenib, for signs or symptoms of non-cutaneous malignancies.

5.2 Hemorrhage

Hemorrhage, including major hemorrhages defined as symptomatic bleeding in a critical area or organ, can occur with COTELLIC.

In Trial 1, the incidence of Grade 3–4 hemorrhages was 1.2% in patients receiving COTELLIC with vemurafenib and 0.8% in patients receiving vemurafenib. Hemorrhage (all grades) was 13% in patients receiving COTELLIC with vemurafenib and 7% in patients receiving vemurafenib. Cerebral hemorrhage occurred in 0.8% of patients receiving COTELLIC with vemurafenib and in none of the patients receiving vemurafenib. Gastrointestinal tract hemorrhage (3.6% vs 1.2%), reproductive system hemorrhage (2.0% vs 0.4%), and hematuria (2.4% vs 0.8%) also occurred at a higher incidence in patients receiving COTELLIC with vemurafenib compared with patients receiving vemurafenib.

In Trial 2, in patients with histiocytic neoplasms, 19% of patients experienced hemorrhage events (all were of grade 1 severity).

Withhold COTELLIC for Grade 3 hemorrhagic events. If improved to Grade 0 or 1 within 4 weeks, resume COTELLIC at a lower dose level. Discontinue COTELLIC for Grade 4 hemorrhagic events and any Grade 3 hemorrhagic events that do not improve [see Dosage and Administration (2.3)].

5.3 Cardiomyopathy

Cardiomyopathy, defined as symptomatic and asymptomatic decline in left ventricular ejection fraction (LVEF), can occur with COTELLIC. The safety of COTELLIC has not been established in patients with a baseline LVEF that is either below institutional lower limit of normal (LLN) or below 50%.

In Trial 1, patients were assessed for decreases in LVEF by echocardiograms or MUGA at baseline, Week 5, Week 17, Week 29, Week 43, and then every 4 to 6 months thereafter while receiving treatment. Grade 2 or 3 decrease in LVEF occurred in 26% of patients receiving COTELLIC with vemurafenib and 19% of patients receiving vemurafenib. The median time to first onset of LVEF decrease was 4 months (range 23 days to 13 months). Of the patients with decreased LVEF, 22% had dose interruption and/or reduction and 14% required permanent discontinuation. Decreased LVEF resolved to above the LLN or within 10% of baseline in 62% of patients receiving COTELLIC with a median time to resolution of 3 months (range: 4 days to 12 months).

In Trial 2, in patients with histiocytic neoplasms, 8% of patients experienced grade 2 ejection fraction decreased and 12% experienced grade 3-4 events. The median time to first onset of LVEF decrease was 29 days (range 22 days to 114 days). Of the patients with decreased LVEF, all had dose interruption and/or reduction and none required permanent discontinuation. Decreased LVEF resolved to above the LLN or within 10% of baseline in 60% of patients receiving COTELLIC with a median time to resolution of 31 days (range: 13 days to 126 days).

Evaluate LVEF prior to initiation, 1 month after initiation, and every 3 months thereafter until discontinuation of COTELLIC. Manage events of left ventricular dysfunction through treatment interruption, reduction, or discontinuation [see Dosage and Administration (2.3)]. In patients restarting COTELLIC after a dose reduction or interruption, evaluate LVEF at approximately 2 weeks, 4 weeks, 10 weeks, and 16 weeks, and then as clinically indicated.

5.4 Severe Dermatologic Reactions

Severe rash and other skin reactions can occur with COTELLIC.

In Trial 1, Grade 3 to 4 rash, occurred in 16% of patients receiving COTELLIC with vemurafenib and in 17% of patients receiving vemurafenib, including Grade 4 rash in 1.6% of patients receiving COTELLIC with vemurafenib and 0.8% of the patients receiving vemurafenib. The incidence of rash resulting in hospitalization was 3.2% in patients receiving COTELLIC with vemurafenib and 2.0% in patients receiving vemurafenib. In patients receiving COTELLIC, the median time to onset of Grade 3 or 4 rash events was 11 days (range: 3 days to 2.8 months). Among patients with Grade 3 or 4 rash events, 95% experienced complete resolution with the median time to resolution of 21 days (range 4 days to 17 months).

In Trial 2, in patients with histiocytic neoplasms, 81% of patients experienced rash events (all were of grade 1-2 severity).

Interrupt, reduce the dose, or discontinue COTELLIC [see Dosage and Administration (2.3)].

5.5 Serous Retinopathy and Retinal Vein Occlusion

Ocular toxicities can occur with COTELLIC, including serous retinopathy (fluid accumulation under layers of the retina).

In Trial 1, ophthalmologic examinations including retinal evaluation were performed pretreatment and at regular intervals during treatment. Symptomatic and asymptomatic serous retinopathy was identified in 26% of patients receiving COTELLIC with vemurafenib. The majority of these events were reported as chorioretinopathy (13%) or retinal detachment (12%). The time to first onset of serous retinopathy events ranged between 2 days to 9 months. The reported duration of serous retinopathy ranged between 1 day to 15 months. One patient in each arm developed retinal vein occlusion.

In Trial 2, in patients with histiocytic neoplasms, 4% experienced grade 2 retinopathy and 4% experienced grade 3 retinal vascular disorder.

Perform an ophthalmological evaluation at regular intervals and any time a patient reports new or worsening visual disturbances. If serous retinopathy is diagnosed, interrupt COTELLIC until visual symptoms improve. Manage serous retinopathy with treatment interruption, dose reduction, or with treatment discontinuation [see Dosage and Administration (2.3)].

5.6 Hepatotoxicity

Hepatotoxicity can occur with COTELLIC.

The incidences of Grade 3 or 4 liver laboratory abnormalities in Trial 1 among patients receiving COTELLIC with vemurafenib compared to patients receiving vemurafenib were: 11% vs. 5% for alanine aminotransferase, 8% vs. 2.1% for aspartate aminotransferase, 1.6% vs. 1.2% for total bilirubin, and 7% vs. 3.3% for alkaline phosphatase [see Adverse Drug Reactions (6.1)]. Concurrent elevation in ALT >3 times the upper limit of normal (ULN) and bilirubin >2 × ULN in the absence of significant alkaline phosphatase >2 × ULN occurred in one patient (0.4%) receiving COTELLIC with vemurafenib and no patients receiving single-agent vemurafenib.

In Trial 2, in patients with histiocytic neoplasms, 9% of the patients receiving COTELLIC experienced grade 3 or 4 aspartate aminotransferase increased and 5% of the patients experienced grade 3 or 4 alanine aminotransferase increased.

Monitor liver laboratory tests before initiation of COTELLIC and monthly during treatment, or more frequently as clinically indicated. Manage Grade 3 and 4 liver laboratory abnormalities with dose interruption, reduction, or discontinuation of COTELLIC [see Dosage and Administration (2.3)].

5.7 Rhabdomyolysis

Rhabdomyolysis can occur with COTELLIC.

In Trial 1, Grade 3 or 4 CPK elevations, including asymptomatic elevations over baseline, occurred in 14% of patients receiving COTELLIC with vemurafenib and 0.5% of patients receiving vemurafenib. The median time to first occurrence of Grade 3 or 4 CPK elevations was 16 days (range: 12 days to 11 months) in patients receiving COTELLIC with vemurafenib; the median time to complete resolution was 15 days (range: 9 days to 11 months). Elevation of serum CPK increase of more than 10 times the baseline value with a concurrent increase in serum creatinine of 1.5 times or greater compared to baseline occurred in 3.6% of patients receiving COTELLIC with vemurafenib and in 0.4% of patients receiving vemurafenib.

Obtain baseline serum CPK and creatinine levels prior to initiating COTELLIC, periodically during treatment, and as clinically indicated. If CPK is elevated, evaluate for signs and symptoms of rhabdomyolysis or other causes. Depending on the severity of symptoms or CPK elevation, dose interruption or discontinuation of COTELLIC may be required [see Dosage and Administration (2.3)].

In Trial 2, in patients with histiocytic neoplasms, 27% of patients experienced grade 2 CPK elevation and 27% of patients experienced grade 3-4 CPK elevation.

5.8 Severe Photosensitivity

Photosensitivity, including severe cases, can occur with COTELLIC.

In Trial 1, photosensitivity was reported in 47% of patients receiving COTELLIC with vemurafenib: 43% of patients with Grades 1 or 2 photosensitivity and the remaining 4% with Grade 3 photosensitivity. Median time to first onset of photosensitivity of any grade was 2 months (range: 1 day to 14 months) in patients receiving COTELLIC with vemurafenib, and the median duration of photosensitivity was 3 months (range: 2 days to 14 months). Among the 47% of patients with photosensitivity reactions on COTELLIC with vemurafenib, 63% experienced resolution of photosensitivity reactions.

Advise patients to avoid sun exposure, wear protective clothing and use a broad-spectrum UVA/UVB sunscreen and lip balm (SPF ≥30) when outdoors. Manage intolerable Grade 2 or greater photosensitivity with dose modifications [see Dosage and Administration (2.3)].

5.9 Embryo-Fetal Toxicity

Based on its mechanism of action and findings from animal reproduction studies, COTELLIC can cause fetal harm when administered to a pregnant woman. In animal reproduction studies, oral administration of cobimetinib in pregnant rats during the period of organogenesis was teratogenic and embryotoxic at doses resulting in exposures [area under the curves (AUCs)] that were 0.9 to 1.4-times those observed in humans at the recommended human dose of 60 mg. Advise pregnant women of the potential risk to a fetus. Advise females of reproductive potential to use effective contraception during treatment with COTELLIC, and for 2 weeks following the final dose of COTELLIC [see Use in Specific Populations (8.1, 8.3), Clinical Pharmacology (12.1)].

6 ADVERSE REACTIONS

The following adverse reactions are discussed in greater detail in other sections of the label:

- New Primary Cutaneous Malignancies [see Warnings and Precautions (5.1)]
- Hemorrhage [see Warnings and Precautions (5.2)]
- Cardiomyopathy [see Warnings and Precautions (5.3)]
- Serious Dermatologic Reactions [see Warnings and Precautions (5.4)]
- Serous Retinopathy and Retinal Vein Occlusion [see Warnings and Precautions (5.5)]
- Hepatotoxicity [see Warnings and Precautions (5.6)]
- Rhabdomyolysis [see Warnings and Precautions (5.7)]
- Severe Photosensitivity [see Warnings and Precautions (5.8)]

6.1 Clinical Trials Experience

Because clinical trials are conducted under widely varying conditions, adverse reaction rates observed in the clinical trials of a drug cannot be directly compared to rates in the clinical trials of another drug and may not reflect the rates observed in practice.

Unresectable or Metastatic Melanoma

The safety of COTELLIC was evaluated in Trial 1, a randomized (1:1), double-blind, active-controlled trial in previously untreated patients with BRAF V600 mutation-positive, unresectable or metastatic melanoma [see Clinical Studies (14)]. All patients received vemurafenib 960 mg twice daily on Days 1–28 and received either COTELLIC 60 mg once daily (n=247) or placebo (n=246) on Days 1–21 of each 28-day treatment cycle until disease progression or unacceptable toxicity. In the COTELLIC plus vemurafenib arm, 66% percent of patients were exposed for greater than 6 months and 24% of patients were exposed for greater than 1 year. Patients with abnormal liver function tests, history of acute coronary syndrome within 6 months, evidence of Class II or greater congestive heart failure (New York Heart Association), active central nervous system lesions, or evidence of retinal pathology were excluded from Trial 1. The demographics and baseline tumor characteristics of patients enrolled in Trial 1 are summarized in Clinical Studies [see Clinical Studies (14)].

In Trial 1, 15% of patients receiving COTELLIC experienced an adverse reaction that resulted in permanent discontinuation of COTELLIC. The most common adverse reactions resulting in permanent discontinuation were liver laboratory abnormalities defined as increased aspartate aminotransferase (AST) (2.4%), increased gamma glutamyltransferase (GGT) (1.6%) and increased alanine aminotransferase (ALT) (1.6%); rash (1.6%); pyrexia (1.2%); and retinal detachment (2%). Among the 247 patients receiving COTELLIC, adverse reactions led to dose interruption or reductions in 55%. The most common reasons for dose interruptions or reductions of COTELLIC were rash (11%), diarrhea (9%), chorioretinopathy (7%), pyrexia (6%), vomiting (6%), nausea (5%), and increased creatine phosphokinase (CPK) (4.9%). The most common (≥20%) adverse reactions with COTELLIC were diarrhea, photosensitivity reaction, nausea, pyrexia, and vomiting.

Table 3. Incidence of Adverse Drug Reactions Occurring in ≥10% (All Grades) of Unresectable or Metastatic Melanoma Patients Receiving COTELLIC with Vemurafenib and at a Higher Incidence [≥5% for All Grades or ≥2% for Grades 3–4 incidence in patients receiving COTELLIC with vemurafenib compared with patients receiving vemurafenib as a single agent] than Patients Receiving Vemurafenib in Trial 1
Adverse reactions | COTELLIC + Vemurafenib (n=247) |  | Placebo + Vemurafenib (n=246)
Adverse reactions | All Grades [NCI CTCAE, v4.0.] (%) | Grades 3–4 (%) | All Grades (%) | Grades 3–4 (%)
GASTROINTESTINAL DISORDERS
Diarrhea | 60 | 6 | 31 | 1
Nausea | 41 | 1 | 25 | 1
Vomiting | 24 | 1 | 13 | 1
Stomatitis [Includes stomatitis, aphthous stomatitis, mouth ulceration, and mucosal inflammation] | 14 | 1 | 8 | 0
SKIN AND SUBCUTANEOUS TISSUE DISORDERS
Photosensitivity reaction [Includes solar dermatitis, sunburn, photosensitivity reaction] | 46 | 4 | 35 | 0
Acneiform dermatitis | 16 | 2 | 11 | 1
GENERAL DISORDERS AND ADMINISTRATION SITE CONDITIONS
Pyrexia | 28 | 2 | 23 | 0
Chills | 10 | 0 | 5 | 0
VASCULAR DISORDERS
Hypertension | 15 | 4 | 8 | 2
Hemorrhage [Includes hemorrhage, rectal hemorrhage, melena, hemorrhoidal hemorrhage, gastrointestinal hemorrhage, hematemesis, hematochezia, gingival bleeding, metrorrhagia, uterine hemorrhage, hemorrhagic ovarian cyst, menometrorrhagia, menorrhagia, vaginal hemorrhage, hemoptysis, pulmonary, cerebral, subarachnoid hemorrhage, subgaleal hematoma, hematuria, epistaxis, contusion, traumatic hematoma, ecchymosis, purpura, nail bed bleeding, ocular, eye, conjunctival, and retinal hemorrhage] | 13 | 1 | 7 | <1
EYE DISORDERS
Vision impaired [Includes vision blurred, visual acuity reduced, visual impairment] | 15 | <1 | 4 | 0
Chorioretinopathy | 13 | <1 | <1 | 0
Retinal detachment [Includes retinal detachment, detachment of retinal pigment epithelium, detachment of macular retinal pigment epithelium] | 12 | 2 | <1 | 0

The following clinically relevant adverse reactions (all grades) of COTELLIC were reported with <10% incidence in Trial 1:

Respiratory, thoracic and mediastinal disorders: Pneumonitis

Table 4. Incidence of Laboratory Abnormalities Occurring in ≥10% (All Grades) or ≥2% (Grades 3–4) of Patients with Unresectable or Metastatic Melanoma in Trial 1 [All the percentages are based on the number of patients who had a baseline result and at least one on-study laboratory test. The laboratory results are available for a total of 233~244 patients for COTELLIC, and 232~243 for vemurafenib, except where indicated.]
Laboratory | COTELLIC + Vemurafenib |  | Placebo + Vemurafenib
Laboratory | All Grades [NCI CTCAE v4.0.] | Grades 3–4 | All Grades | Grades 3–4
Laboratory | % | % | % | %
Chemistry
Increased creatinine | 100 | 3.3 | 100 | 0.4
Increased AST | 73 | 8 | 44 | 2.1
Increased ALT | 68 | 11 | 55 | 5
Increased alkaline phosphatase | 71 | 7 | 56 | 3.3
Increased creatine phosphokinase [Increase creatine phosphokinase, n=213 for COTELLIC and 217 for vemurafenib.] | 79 | 14 | 16 | 0.5
Hypophosphatemia | 68 | 12 | 38 | 6
Increased GGT | 65 | 21 | 61 | 17
Hyponatremia | 38 | 6 | 33 | 2.1
Hypoalbuminemia | 42 | 0.8 | 20 | 0.4
Hypokalemia | 25 | 4.5 | 17 | 3.3
Hyperkalemia | 26 | 2.9 | 15 | 0.4
Hypocalcemia | 24 | 0.4 | 10 | 1.7
Hematology
Anemia | 69 | 2.5 | 57 | 3.3
Lymphopenia [Lymphopenia, n=185 for COTELLIC, and 181 for vemurafenib.] | 73 | 10 | 55 | 8
Thrombocytopenia | 18 | 0 | 10 | 0
AST - aspartate aminotransferase, ALT - alanine aminotransferase, GGT - gamma-glutamyltransferase

Histiocytic Neoplasms

The safety of COTELLIC was evaluated in Trial 2, a single-center single-arm trial in patients with histiocytic neoplasms [see Clinical Studies (14)]. In Trial 2, 26 patients with histiocytic neoplasms received COTELLIC 60 mg once daily for 21 days on, then 7 days off, in a 28-day treatment cycle. The median treatment duration was 10.7 months. Table 5 presents adverse reactions in at least 15% of patients reported with histiocytic neoplasms treated with COTELLIC. Table 6 presents laboratory abnormalities of grades ≥3 reported in patients with histiocytic neoplasms treated COTELLIC.

In Trial 2, 4 patients (15%) receiving COTELLIC experienced an adverse reaction that resulted in permanent discontinuation of COTELLIC. One patient discontinued due to worsening of underlying dyspnea and hypoxia; one patient discontinued due to retinal vascular disorder; one patient discontinued due to hyponatremia; and the other patient discontinued due to pneumonia.

Table 5 Incidence of Adverse Reactions Reported Occurring in ≥15% (All Grades) or Any Percentage (Grade ≥3) in Patients with Histiocytic Neoplasms Treated with COTELLIC in Trial 2
Body Systems Adverse reactions | All Grades [NCI CTCAE v4.0.] (%) (n=26) | Grades ≥3 (%) (n=26)
GASTROINTESTINAL DISORDERS
Diarrhea | 62 | 8
Nausea | 46 | 0
Dyspepsia [Gastritis, and gastroesophageal reflux disease.] | 27 | 0
Vomiting | 27 | 0
Dry Mouth | 15 | 0
Oral pain [Oral dysesthesia and oropharyngeal pain.] | 15 | 0
GENERAL DISORDERS AND ADMINISTRATION SITE CONDITIONS
Fatigue [Malaise] | 42 | 0
Edema [Facial edema, edema genital, edema peripheral, periorbital edema, and lymphoedema.] | 42 | 4
Pain | 15 | 0
INFECTIONS AND INFESTATIONS
Infections [Influenza like illness, mucosal infection, paronychia, pharyngitis, pneumonia, bronchitis, sepsis, sinusitis, skin infection, tooth infection, upper respiratory tract infection., and urinary tract infection.] | 62 | 23
Urinary tract infection | 23 | 8
Pulmonary infections [Pneumonia and bronchitis.] | 19 | 12
INJURY, POISONING AND PROCEDURAL COMPLICATIONS
Fall | 15 | 4
INVESTIGATIONS
Decreased Ejection Fraction | 19 | 12
RENAL AND URINARY
Acute kidney injury | 15 | 12
RESPIRATORY, THORACIC AND MEDIASTINAL DISORDERS
Dyspnea | 27 | 15
Cough | 15 | 0
SKIN AND SUBCUTANEOUS TISSUE DISORDERS
Acneiform dermatitis | 65 | 0
Dry skin | 31 | 0
Maculo-papular rash | 31 | 0
Pruritus | 31 | 4
VASCULAR DISORDERS
Hemorrhage [Epistaxis, contusion, purpura, hematoma, and rectal hemorrhage.] | 19 | 0
Hypertension | 15 | 4

The following clinically relevant adverse reactions (all grades) of COTELLIC were reported with <15% incidence in Trial 2:

Eye disorders: Vision blurred (12%), retinal vascular disorder (4%) and retinopathy (4%).

Gastrointestinal disorders: Stomatitis (12%)

Nervous system disorders: Headache (12%)

Respiratory, thoracic, and mediastinal disorders: Hypoxia (12%), pulmonary edema (4%), and respiratory failure (8%).

Table 6. Incidence of Grade ≥3 Laboratory Abnormalities Occurring in Patients with Histiocytic Neoplasms Treated with COTELLIC in Trial 2 [All the percentages are based on the number of patients who had a baseline result and at least one on-study laboratory test.]
 | Grades 3–4 [NCI CTCAE v4.0] %
Chemistry
Increased blood creatine phosphokinase | 27
Hyponatremia | 18
Hypokalemia | 12
Increased blood creatinine | 9
Increased AST | 9
Hypocalcemia | 9
Increased ALT | 5
Hematology
Lymphopenia | 27
Leukopenia | 9
Anemia | 8
Neutropenia | 5
AST - aspartate aminotransferase, ALT - alanine aminotransferase

7 DRUG INTERACTIONS

7.1 Effect of Strong or Moderate CYP3A Inhibitors on COTELLIC

Coadministration of COTELLIC with itraconazole (a strong CYP3A4 inhibitor) increased cobimetinib systemic exposure by 6.7-fold. Avoid concurrent use of COTELLIC and strong or moderate CYP3A inhibitors. If concurrent short term (14 days or less) use of moderate CYP3A inhibitors including certain antibiotics (e.g., erythromycin, ciprofloxacin) is unavoidable for patients who are taking COTELLIC 60 mg, reduce COTELLIC dose to 20 mg. After discontinuation of a moderate CYP3A inhibitor, resume COTELLIC at the previous dose [see Dosage and Administration (2.3) and Clinical Pharmacology (12.3)]. Use an alternative to a strong or moderate CYP3A inhibitor in patients who are taking a reduced dose of COTELLIC (40 or 20 mg daily) [see Dosage and Administration (2.3) and Clinical Pharmacology (12.3)].

7.2 Effect of Strong or Moderate CYP3A Inducers on COTELLIC

Coadministration of COTELLIC with a strong CYP3A inducer may decrease cobimetinib systemic exposure by more than 80% and reduce its efficacy. Avoid concurrent use of COTELLIC and strong or moderate CYP3A inducers including but not limited to carbamazepine, efavirenz, phenytoin, rifampin, and St. John's Wort [see Clinical Pharmacology (12.3)].

8 USE IN SPECIFIC POPULATIONS

8.1 Pregnancy

Risk Summary

Based on findings from animal reproduction studies and its mechanism of action, COTELLIC can cause fetal harm when administered to a pregnant woman [see Clinical Pharmacology (12.1)]. There are no available data on the use of COTELLIC during pregnancy. In animal reproduction studies, oral administration of cobimetinib in pregnant rats during organogenesis was teratogenic and embryotoxic at exposures (AUC) that were 0.9 to 1.4-times those observed in humans at the recommended human dose of 60 mg [see Data]. Advise pregnant women of the potential risk to a fetus.

In the U.S. general population, the estimated background risk of major birth defects and miscarriage in clinically recognized pregnancies is 2–4% and 15–20%, respectively.

Data

Animal Data

Administration of cobimetinib to pregnant rats during the period of organogenesis resulted in increased post-implantation loss, including total litter loss, at exposures (AUC) of 0.9–1.4 times those in humans at the recommended dose of 60 mg. Post-implantation loss was primarily due to early resorptions. Fetal malformations of the great vessels and skull (eye sockets) occurred at the same exposures.

8.2 Lactation

Risk Summary

There is no information regarding the presence of cobimetinib in human milk, effects on the breastfed infant, or effects on milk production. Because of the potential for serious adverse reactions in a breastfed infant, advise a nursing woman not to breastfeed during treatment with COTELLIC and for 2 weeks after the final dose.

8.3 Females and Males of Reproductive Potential

Contraception

Females

COTELLIC can cause fetal harm when administered to a pregnant woman [see Use in Specific Populations (8.1)]. Advise females of reproductive potential to use effective contraception during treatment with COTELLIC and for 2 weeks after the final dose of COTELLIC.

Infertility

Females and Males

Based on findings in animals, COTELLIC may reduce fertility in females and males of reproductive potential [see Nonclinical Toxicology (13.1)].

8.4 Pediatric Use

The safety and effectiveness of COTELLIC have not been established in pediatric patients.

The safety and effectiveness of COTELLIC were assessed, but not established, in a multi-center, open-label, dose-escalation study in 55 pediatric patients aged 2 to 17 years with solid tumors [NCT02639546]. No new safety events were observed in pediatric patients in this trial.

Exposure in pediatric patients who received COTELLIC at the maximum tolerated dosage were lower than those previously observed in adults who received the approved recommended dosage.

Juvenile Animal Data

In a 4-week juvenile rat toxicology study, daily oral doses of 3 mg/kg (approximately 0.13–0.5 times the adult human AUC at the recommended dose of 60 mg) between postnatal Days 10–17 (approximately equivalent to ages 1–2 years in humans) were associated with mortality, the cause of which was not defined.

8.5 Geriatric Use

Clinical studies of COTELLIC did not include sufficient numbers of patients aged 65 years and older to determine whether they respond differently from younger patients.

8.6 Hepatic Impairment

Adjustment in the starting dose of COTELLIC is not required in patients with mild (Child-Pugh score A), moderate (Child-Pugh B) or severe (Child-Pugh C) hepatic impairment [see Clinical Pharmacology (12.3)].

8.7 Renal Impairment

No dedicated pharmacokinetic trial in patients with renal impairment has been conducted. Dose adjustment is not recommended for mild to moderate renal impairment (CLcr 30 to 89 mL/min) based on the results of the population pharmacokinetic analysis. A recommended dose has not been established for patients with severe renal impairment [see Clinical Pharmacology (12.3)].

10 OVERDOSAGE

There is no information on overdosage of COTELLIC.

11 DESCRIPTION

Cobimetinib fumarate is a kinase inhibitor. The chemical name is (S)-[3,4-difluoro-2-(2-fluoro-4-iodophenylamino)phenyl] [3-hydroxy-3-(piperidin-2-yl)azetidin-1-yl]methanone hemifumarate. It has a molecular formula C46H46F6I2N6O8 (2 C21H21F3IN3O2 ∙ C4H4O4) with a molecular mass of 1178.71 as a fumarate salt. Cobimetinib fumarate has the following chemical structure:

Cobimetinib is a fumarate salt appearing as white to off-white solid and exhibits a pH dependent solubility.

COTELLIC (cobimetinib) tablets are supplied as white, round, film-coated 20 mg tablets for oral administration, debossed on one side with "COB". Each 20 mg tablet contains 22 mg of cobimetinib fumarate, which corresponds to 20 mg of the cobimetinib free base.

The inactive ingredients of COTELLIC are: Tablet Core: microcrystalline cellulose, lactose monohydrate, croscarmellose sodium, magnesium stearate. Coating: polyvinyl alcohol, titanium dioxide, polyethylene glycol 3350, talc.

12 CLINICAL PHARMACOLOGY

12.1 Mechanism of Action

Cobimetinib is a reversible inhibitor of mitogen-activated protein kinase (MAPK)/extracellular signal regulated kinase 1 (MEK1) and MEK2. MEK proteins are upstream regulators of the extracellular signal-related kinase (ERK) pathway, which promotes cellular proliferation. BRAF V600E and K mutations result in constitutive activation of the BRAF pathway which includes MEK1 and MEK2. In mice implanted with tumor cell lines expressing BRAF V600E, cobimetinib inhibited tumor cell growth.

Cobimetinib and vemurafenib target two different kinases in the RAS/RAF/MEK/ERK pathway. Compared to either drug alone, coadministration of cobimetinib and vemurafenib resulted in increased apoptosis in vitro and reduced tumor growth in mouse implantation models of tumor cell lines harboring BRAF V600E mutations. Cobimetinib also prevented vemurafenib-mediated growth enhancement of a wild-type BRAF tumor cell line in an in vivo mouse implantation model.

12.2 Pharmacodynamics

Cardiac Electrophysiology

Clinically relevant QT prolongation has been reported with vemurafenib, further QTc prolongation was not observed when cobimetinib 60 mg daily was co-administered with vemurafenib. Monitor ECG and electrolytes before initiating treatment and routinely during treatment with cobimetinib, when administered with vemurafenib. Review the Full Prescribing Information for vemurafenib for details.

12.3 Pharmacokinetics

The pharmacokinetics of cobimetinib was studied in healthy subjects and cancer patients. Cobimetinib exhibits linear pharmacokinetics in the dose range of 3.5 to 100 mg (i.e., 0.06 to 1.7 times the recommended dosage). Following oral administration of COTELLIC 60 mg once daily, steady-state was reached by 9 days with a mean accumulation ratio of 2.4-fold (44% CV).

Absorption

Following oral dosing of 60 mg once daily in cancer patients, the median time to achieve peak plasma levels (Tmax) was 2.4 (range:1–24) hours, geometric mean steady-state AUC0-24h was 4340 ng∙h/mL (61% CV) and Cmax was 273 ng/mL (60% CV). The absolute bioavailability of COTELLIC was 46% (90% CI: 40%, 53%) in healthy subjects. A high-fat meal (comprised of approximately 150 calories from protein, 250 calories from carbohydrate, and 500–600 calories from fat) had no effect on cobimetinib AUC and Cmax after a single 20 mg COTELLIC was administered to healthy subjects.

Distribution

Cobimetinib is 95% bound to human plasma proteins in vitro, independent of drug concentration. No preferential binding to human red blood cells was observed (blood to plasma ratio of 0.93). The estimated apparent volume of distribution was 806 L in cancer patients based on a population PK analysis.

Elimination

Following oral administration of COTELLIC 60 mg once daily in cancer patients, the mean elimination half-life (t1/2) was 44 (range: 23–70) hours and the mean apparent clearance (CL/F) was 13.8 L/h (61% CV).

Metabolism

CYP3A oxidation and UGT2B7 glucuronidation were the major pathways of cobimetinib metabolism in vitro. Following oral administration of a single 20 mg radiolabeled cobimetinib dose, no oxidative metabolites >10% of total circulating radioactivity were observed.

Excretion

Following oral administration of a single 20 mg radiolabeled cobimetinib dose, 76% of the dose was recovered in the feces (with 6.6% as unchanged drug) and 17.8% of the dose was recovered in the urine (with 1.6% as unchanged drug).

Specific Populations

Age, Sex, and Race/Ethnicity: Based on the population pharmacokinetic analysis, age (19–88 years), sex, or race/ethnicity does not have a clinically important effect on the systemic exposure of cobimetinib.

Hepatic Impairment

Following a single 10 mg COTELLIC dose, the geometric mean total cobimetinib exposure (AUCinf) values were similar in subjects with mild or moderate hepatic impairment and was decreased by 31% in subjects with severe hepatic impairment compared to subjects with normal hepatic function. [see Use in Specific Populations (8.6)].

Renal Impairment

Cobimetinib undergoes minimal renal elimination. Cobimetinib exposures were similar in 151 patients with mild renal impairment (CLcr 60 to 89 mL/min), 48 patients with moderate renal impairment (CLcr 30 to 59 mL/min) and 286 patients with normal renal function (CLcr ≥90 mL/min) [see Use in Specific Populations (8.7)].

Drug Interaction Studies

Vemurafenib: Coadministration of COTELLIC 60 mg once daily and vemurafenib 960 mg twice daily resulted in no clinically relevant pharmacokinetic drug interactions.

Effect of Strong and Moderate CYP3A Inhibitors on Cobimetinib: In vitro studies show that cobimetinib is a substrate of CYP3A. Coadministration of itraconazole (a strong CYP3A inhibitor) 200 mg once daily for 14 days with a single 10 mg cobimetinib dose increased mean cobimetinib AUC (90% CI) by 6.7-fold (5.6, 8.0) and mean Cmax (90% CI) by 3.2-fold (2.7, 3.7) in 15 healthy subjects. Simulations showed that predicted steady-state concentrations of cobimetinib at a reduced dose of 20 mg administered concurrently with short-term (less than 14 days) treatment of a moderate CYP3A inhibitor were similar to observed steady-state concentrations of cobimetinib at the 60 mg dose alone [see Drug Interactions (7.1)].

Effect of Strong and Moderate CYP3A Inducers on Cobimetinib: Based on simulations, cobimetinib exposures would decrease by 83% when coadministered with a strong CYP3A inducer and by 73% when coadministered with a moderate CYP3A inducer [see Drug Interactions (7.2)].

Effect of Cobimetinib on CYP Substrates: Coadministration of cobimetinib 60 mg once daily for 15 days with a single 30 mg dose of dextromethorphan (sensitive CYP2D6 substrate) or a single 2 mg dose of midazolam (sensitive CYP3A substrate) to 20 patients with solid tumors did not change dextromethorphan or midazolam systemic exposure. In vitro data indicated that cobimetinib may inhibit CYP3A and CYP2D6. Cobimetinib at clinically relevant concentrations is not an inhibitor of CYP1A2, 2B6, 2C8, 2C9 and 2C19 or inducer of CYP1A2, 2B6 and 3A4.

Effect of Transporters on Cobimetinib: Cobimetinib is a substrate of efflux transporter P-glycoprotein (P-gp), but is not a substrate of Breast Cancer Resistance Protein (BCRP), Organic Anion Transporting Polypeptide (OATP1B1 or OATP1B3) or Organic Cation Transporter (OCT1) in vitro. Drugs that inhibit P-gp may increase cobimetinib concentrations.

Effect of Cobimetinib on Transporters: In vitro data suggest that cobimetinib at clinically relevant concentrations does not inhibit P-gp, BCRP, OATP1B1, OATP1B3, OCT1, OAT1, OAT3, or OCT2.

Effect of Gastric Acid Reducing Drugs on Cobimetinib: Coadministration of a proton pump inhibitor, rabeprazole 20 mg once daily for 5 days, with a single dose of 20 mg COTELLIC under fed and fasted conditions did not result in a clinically important change in cobimetinib exposure.

13 NONCLINICAL TOXICOLOGY

13.1 Carcinogenesis, Mutagenesis, Impairment of Fertility

Carcinogenicity studies with cobimetinib have not been conducted. Cobimetinib was not genotoxic in studies evaluating reverse mutations in bacteria, chromosomal aberrations in mammalian cells, and micronuclei in bone marrow of rats.

No dedicated fertility studies have been performed with cobimetinib in animals; however, effects on reproductive tissues observed in general toxicology studies conducted in animals suggest that there is potential for cobimetinib to impair fertility. In female rats, degenerative changes included increased apoptosis/necrosis of corpora lutea and vaginal epithelial cells at cobimetinib doses approximately twice those in humans at the clinically recommended dose of 60 mg based on body surface area. In male dogs, testicular degeneration occurred at exposures as low as approximately 0.1 times the exposure in humans at the clinically recommended dose of 60 mg.

14 CLINICAL STUDIES

14.1 Unresectable or Metastatic Melanoma

The safety and efficacy of COTELLIC was established in a multicenter, randomized (1:1), double-blinded, placebo-controlled trial conducted in 495 patients with previously untreated, BRAF V600 mutation-positive, unresectable or metastatic, melanoma. The presence of BRAF V600 mutation was detected using the cobas® 4800 BRAF V600 mutation test. All patients received vemurafenib 960 mg orally twice daily on days 1–28 and were randomized to receive COTELLIC 60 mg or matching placebo orally once daily on days 1–21 of an every 28-day cycle. Randomization was stratified by geographic region (North America vs. Europe vs. Australia/New Zealand/others) and disease stage (unresectable Stage IIIc, M1a, or M1b vs. Stage M1c). Treatment continued until disease progression or unacceptable toxicity. Patients randomized to receive placebo were not offered COTELLIC at the time of disease progression.

The major efficacy outcome was investigator-assessed progression-free survival (PFS) per RECIST v1.1. Additional efficacy outcomes were investigator-assessed confirmed objective response rate, overall survival, PFS as assessed by blinded independent central review, and duration of response.

The median age of the study population was 55 years (range 23 to 88 years), 58% of patients were male, 93% were White and 5% had no race reported, 60% had stage M1c disease, 72% had a baseline ECOG performance status of 0, 45% had an elevated baseline serum lactate dehydrogenase (LDH), 10% had received prior adjuvant therapy, and <1% had previously treated brain metastases. Patients with available tumor samples were retrospectively tested using next generation sequencing to further classify mutations as V600E or V600K; test results were obtained on 81% of randomized patients. Of these, 86% were identified as having a V600E mutation and 14% as having a V600K mutation.

Efficacy results are summarized in Table 7 and Figure 1.

Table 7 Efficacy Results from Trial 1
 | COTELLIC + Vemurafenib (n=247) | Placebo + Vemurafenib (n=248)
Progression-Free Survival (Investigator-Assessed)
Number of Events (%) | 143 (58%) | 180 (73%)
Progression | 131 | 169
Death | 12 | 11
Median PFS, months (95% CI) | 12.3 (9.5, 13.4) | 7.2 (5.6, 7.5)
Hazard Ratio (95% CI) | 0.56 (0.45, 0.70)
p-value (stratified log-rank test) | <0.001
Overall Survival [Based on the final overall survival analysis, conducted after 16 months from the PFS primary analysis]
Number of Deaths (%) | 114 (46.2%) | 141 (56.9%)
Median OS, months (95% CI) | 22.3 (20.3, NE) | 17.4 (15.0, 19.8)
Hazard Ratio (95% CI) | 0.69 (0.54,0.88)
p -value (stratified log-rank test) | 0.0032
Objective Response Rate
Objective Response Rate | 70% | 50%
(95% CI) | (64%, 75%) | (44%, 56%)
Complete Response | 16% | 10%
Partial Response | 54% | 40%
p-value | <0.001
Median Duration of Response, months (95% CI) | 13.0 (11.1, 16.6) | 9.2 (7.5, 12.8)
CI - Confidence Intervals; NE - not estimable

Figure 1 Kaplan-Meier Curves of Overall Survival

The effect on PFS was also supported by analysis of PFS based on the assessment by blinded independent review. A trend favoring the COTELLIC with vemurafenib arm was observed in exploratory subgroup analyses of PFS, OS, and ORR in both BRAF V600 mutation subtypes (V600E or V600K) in the 81% of patients in this trial where BRAF V600 mutation type was determined.

14.2 Histiocytic Neoplasms

A single-center, single-arm trial (Trial 2) was conducted to evaluate the efficacy, safety, and tolerability of COTELLIC as a single agent in adult patients with histologically confirmed histiocytic neoplasms of any mutational status. Patients with documented BRAF V600E mutations were enrolled if they were unable to access a BRAF inhibitor or discontinued a BRAF inhibitor due to toxicity. Enrolled patients had multi-system disease, recurrent or refractory disease, or single-system disease that is unlikely to benefit from conventional therapies, based on best available evidence.

The trial included 26 patients with histiocytic neoplasms including Langerhans Cell Histiocytosis (n=4), Rosai-Dorfman Disease (n=4), Erdheim-Chester Disease (n=13), Xanthogranuloma (n=2) and Mixed Histiocytosis (n=3). Patients with BRAF V600 mutant positive (n=6) and BRAF V600 Wild type (n=20) received COTELLIC. Twenty-one patients (81%) had received prior systemic therapies. The median age was 50.5 years (range, 18 to 79 years). Sixty-five percent of patients were men (n=17) and 35% were women (n=9). The majority of patients were White (85%), 8% were Black or African American and 4% were Asian; 96% were neither Hispanic nor Latino.

Patients were treated with COTELLIC 60 mg once daily for 21 days on, then 7 days off, in a 28-day treatment cycle (n=26). Eighteen patients required a dose reduction to 40 mg, and five patients required an additional dose reduction to 20 mg. The median duration of treatment following a dose reduction to 40 mg and 20 mg was 6.6 months and 3.9 months respectively.

The major efficacy outcome was best overall response rate (BORR), maintained on two occasions at least four weeks apart, as assessed by the investigator using the PET Response Criteria (PRC). Other clinical outcomes included PRC-based duration of response (DOR), and BORR maintained on two occasions at least four weeks apart, as assessed by investigator using RECIST v1.1.

The median duration of follow-up was 11.4 months (range, 0.2 to 36.8 months). The median time to PRC-based response was 2.0 (range, 0.2 to 17.3 months). The median PRC-based DOR was 31 months (range, 2 to 31 months). See Table 8 below for efficacy results.

Table 8 Efficacy of COTELLIC in patients with Histiocytic neoplasms (Trial 2)
Response | PET Response, [Complete Response by PRC was defined as a normalization of all lesions' (target and non-target) standardized uptake values (SUV) to background SUVliver (or SUVbrain for brain lesions only)] , [Partial Response by PRC was defined as a ≥50% decrease from baseline in sum of SUV of all target lesions relative to SUVliver (or SUVbrain for brain lesions only)] Enrolled Patients (n=26) [24 PET-evaluable patients out of 26 enrolled patients. 1 patient had missing baseline scan. 1 patient had short follow-up duration (not enrolled at least 16 weeks prior to the clinical cutoff date (CCOD)] | RECIST Response, Enrolled Patients (n=26) [19 RECIST-evaluable patients out of 26 enrolled patients. 6 patients had missing baseline scans; these patients had lesions that were not measurable by RECIST 1.1 definition. 1 patient had short follow-up duration (not enrolled at least 16 weeks prior to CCOD)]
Overall response rate, n (%) | 20 (76.9%) | 12 (46.2%)
(95% Clopper-Pearson CI) | (56.4, 91) | (26.6, 66.6)
Best Response, n (%)
Complete Response | 16 (61.5%) | 3 (11.5%)
Partial Response | 4 (15.4%) | 9 (34.6%)

16 HOW SUPPLIED/STORAGE AND HANDLING

COTELLIC (cobimetinib) is supplied as 20 mg film-coated tablets debossed on one side with "COB". COTELLIC tablets are available in bottles of 63 tablets.

NDC 50242-717-01

STORAGE AND HANDLING

Storage and Stability: Store at room temperature below 30°C (86°F).

17 PATIENT COUNSELING INFORMATION

Advise the patient to read the FDA-approved patient labeling (Patient Information).

Inform patients of the following:

New primary cutaneous malignancies: Advise patients to contact their health care provider immediately for change in or development of new skin lesions [see Warnings and Precautions (5.1)].

Hemorrhage: Instruct patients to contact their healthcare provider to seek immediate medical attention for signs or symptoms of unusual severe bleeding or hemorrhage [see Warnings and Precautions (5.2)].

Cardiomyopathy: Advise patients to report any history of cardiac disease and of the requirement for cardiac monitoring prior to and during COTELLIC administration. Instruct patients to immediately report any signs or symptoms of left ventricular dysfunction to their healthcare provider [see Warnings and Precautions (5.3)].

Serious dermatologic reactions: Instruct patients to contact their healthcare provider to immediately report severe skin changes [see Warnings and Precautions (5.4)].

Serous retinopathy and retinal vein occlusion: Instruct patients to immediately contact their healthcare provider if they experience any changes in their vision [see Warnings and Precautions (5.5)].

Hepatotoxicity: Advise patients that treatment with COTELLIC requires monitoring of their liver function. Instruct patients to report any signs or symptoms of liver dysfunction [see Warnings and Precautions (5.6)].

Rhabdomyolysis: Instruct patients to report any signs and symptoms of muscle pain or weakness to their healthcare provider [see Warnings and Precautions (5.7)].

Severe photosensitivity: Advise patients to avoid sun exposure, wear protective clothing, and use broad spectrum UVA/UVB sunscreen and lip balm (SPF ≥30) when outdoors [see Warnings and Precautions (5.8)].

Embryo-fetal toxicity: Advise females of reproductive potential of the potential risk to a fetus. Advise females to contact their healthcare provider if they become pregnant, or if pregnancy is suspected, during treatment with COTELLIC [see Warnings and Precautions (5.9), Use in Specific Populations (8.1)].

Females of reproductive potential: Advise females of reproductive potential to use effective contraception during treatment with COTELLIC and for at least 2 weeks after the final dose of COTELLIC [see Use in Specific Populations (8.3)].

Lactation: Advise females not to breastfeed during treatment with COTELLIC and for 2 weeks after the final dose [see Use in Specific Populations (8.2)].

Distributed by:

Genentech USA, Inc.
A Member of the Roche Group
1 DNA Way
South San Francisco, CA 94080-4990

COTELLIC® is a registered trademark of Genentech, Inc.
© 2023 Genentech, Inc. All rights reserved.

PATIENT INFORMATION
COTELLIC® (co-TELL-ic)
(cobimetinib)
tablet

Important: If your healthcare provider prescribes vemurafenib, also read the Medication Guide that comes with vemurafenib.

What is COTELLIC?

COTELLIC is a prescription medicine that is used:

- in combination with vemurafenib to treat adults with a type of skin cancer called melanoma:
  - that has spread to other parts of the body (metastatic) or cannot be removed by surgery (unresectable), and
  - that has a certain type of abnormal "BRAF" gene
- alone to treat adults with a group of blood cancers called histiocytic neoplasms

Your healthcare provider will perform a test to make sure that COTELLIC is right for you.

It is not known if COTELLIC is safe and effective in children under 18 years of age.

Before you take COTELLIC, tell your healthcare provider about all of your medical conditions, including if you:

- have skin problems or a history of skin problems, other than skin cancer (melanoma)
- have bleeding problems or have any medical conditions or take any medicines that increase your risk of bleeding
- have heart problems
- have eye problems
- have liver problems
- have muscle problems
- are pregnant or plan to become pregnant. COTELLIC can harm your unborn baby.
  - Females who are able to become pregnant should use effective birth control (contraception) during treatment with COTELLIC and for 2 weeks after the final dose of COTELLIC.
  - Talk to your healthcare provider about birth control methods that may be right for you.
  - Tell your healthcare provider right away if you become pregnant or think you are pregnant during treatment with COTELLIC.
- are breastfeeding or plan to breastfeed. It is not known if COTELLIC passes into your breast milk. Do not breastfeed during treatment with COTELLIC and for 2 weeks after the final dose. Talk to your healthcare provider about the best way to feed your baby during this time.

Tell your healthcare provider about all the medicines you take, including prescription and over-the-counter medicines, vitamins, and herbal supplements. Certain medicines may affect the blood levels of COTELLIC.

Know the medicines you take. Keep a list of them to show your healthcare provider and pharmacist when you get a new medicine.

How should I take COTELLIC?

- Take COTELLIC exactly as your healthcare provider tells you. Do not change your dose or stop taking COTELLIC unless your healthcare provider tells you to.
- Take COTELLIC one time a day for 21 days, followed by 7 days off treatment, to complete a 28-day treatment cycle.
- Take COTELLIC with or without food.
- If you miss a dose of COTELLIC or vomit after taking your dose, take your next dose as scheduled.

What should I avoid during treatment with COTELLIC?

Avoid sunlight during treatment with COTELLIC. COTELLIC can make your skin sensitive to sunlight. You may burn more easily and get severe sunburns. To help protect against sunburn:

- When you go outside, wear clothes that protect your skin, including your head, face, hands, arms, and legs.
- Use lip balm and a broad-spectrum sunscreen with SPF 30 or higher.

What are the possible side effects of COTELLIC?
COTELLIC may cause serious side effects, including:

- Risk of new skin cancers. COTELLIC may cause new skin cancers (cutaneous squamous cell carcinoma, keratoacanthoma, or basal cell carcinoma).

Check your skin regularly and tell your healthcare provider right away if you have any skin changes including:

- new wart
- skin sore or reddish bump that bleeds or does not heal
- change in size or color of a mole

Your healthcare provider should check your skin before you start taking COTELLIC, and every 2 months during treatment with COTELLIC. Your healthcare provider may continue to check your skin for 6 months after you stop taking COTELLIC. Your healthcare provider should also check for cancers that may not occur on the skin. Tell your healthcare provider about any new symptoms that develop during treatment with COTELLIC and vemurafenib.

- Bleeding problems. COTELLIC can cause serious bleeding problems.
  Call your healthcare provider and get medical attention right away if you get any signs of bleeding, including:

- red or black stools (looks like tar)
- blood in your urine
- headaches
- cough up or vomit blood

- stomach (abdominal) pain
- unusual vaginal bleeding
- dizziness or weakness

- Heart problems. Your healthcare provider should do tests before and during treatment to check your heart function. Tell your healthcare provider if you get any of these signs and symptoms of heart problems:

- persistent coughing or wheezing
- shortness of breath
- swelling of your ankles and feet

- tiredness
- increased heart rate

- Severe rash. Tell your healthcare provider right away if you get any of these symptoms:
  - a rash that covers a large area of your body
  - blisters
  - peeling skin
- Eye problems. Tell your healthcare provider right away if you get any of these symptoms:

- blurred vision
- partly missing vision or loss of vision

- see halos
- any other vision changes

Your healthcare provider should check your eyes if you notice any of the symptoms above.

- Liver problems. Your healthcare provider should do blood tests to check your liver function before and during treatment. Tell your healthcare provider right away if you get any of these symptoms:

- yellowing of your skin or the white of your eyes
- dark or brown (tea color) urine
- nausea or vomiting

- feeling tired or weak
- loss of appetite

- Muscle problems (rhabdomyolysis). COTELLIC can cause muscle problems that can be severe. Treatment with COTELLIC may increase the level of an enzyme in your blood called creatine phosphokinase (CPK) and may be a sign of muscle damage. Your healthcare provider should do a blood test to check your levels of CPK before and during treatment. Tell your healthcare provider right away if you get any of these symptoms:

- muscle aches or pain
- muscle spasms and weakness

- dark, reddish urine

- Skin Sensitivity to sunlight (photosensitivity). Skin sensitivity to sunlight during treatment with COTELLIC is common and can sometimes be severe. Tell your healthcare provider if you get any of these symptoms:

- red, painful, itchy skin that is hot to touch
- sun rash
- skin irritation

- bumps or tiny papules
- thicken, dry, wrinkled skin

See "What should I avoid during treatment with COTELLIC?" for information on protecting your skin during treatment with COTELLIC.

The most common side effects of COTELLIC in adults with unresectable or metastatic melanoma include:

- diarrhea
- sensitivity to sunlight
- nausea

- fever
- vomiting

The most common side effects of COTELLIC in adults with histiocytic neoplasms include:

- acne-like (red and pus filled) bumps on face, scalp, chest or upper back
- diarrhea
- any infection
- tiredness
- nausea
- swelling of arms, legs or feet or any other parts of your body

- dry skin
- rash with both flat and raised reddened areas on your skin
- itching
- indigestion or heartburn
- vomiting
- urinary tract infection
- lung problems

Your healthcare provider will do blood tests during treatment with COTELLIC. The most common changes to blood tests include:

- increased blood level of creatinine
- increased blood levels of liver enzymes (GGT, ALT, or AST)
- increased blood level of enzyme from muscle (creatine phosphokinase)
- decreased blood level of phosphate, albumin, sodium, potassium or calcium
- increased level of liver or bone enzyme (alkaline phosphatase)
- decreased blood level of a type of white blood cell (lymphocytes)
- decreased blood level of red blood counts
- increased blood level of potassium

COTELLIC may cause fertility problems in males and females, which may affect your ability to have a child. Talk to your healthcare provider if this is a concern for you.
These are not all of the possible side effects of COTELLIC.

Call your doctor for medical advice about side effects. You may report side effects to FDA at 1-800-FDA-1088.

You may also report side effects to Genentech at 1-888-835-2555.

How should I store COTELLIC?

- Store COTELLIC at room temperature below 86°F (30°C).

Keep COTELLIC and all medicine out of the reach of children.

General information about the safe and effective use of COTELLIC

Medicines are sometimes prescribed for purposes other than those listed in a Patient Information Leaflet. Do not use COTELLIC for a condition for which it was not prescribed. Do not give COTELLIC to other people, even if they have the same symptoms that you have. It may harm them. You can ask your healthcare provider or pharmacist for information about COTELLIC that is written for health professionals.

What are the ingredients in COTELLIC?

Active ingredient: cobimetinib fumarate

Inactive ingredients:

Tablet Core: microcrystalline cellulose, lactose monohydrate, croscarmellose sodium, magnesium stearate

Coating: polyvinyl alcohol, titanium dioxide, polyethylene glycol 3350, talc

Distributed by: Genentech USA, Inc., A Member of the Roche Group, 1 DNA Way, South San Francisco, CA 94080-4990.

COTELLIC® is a registered trademark of Genentech, Inc.

©2022 Genentech, Inc. All rights reserved. For more information go to www.COTELLIC.com or call 1-877-436-3683.

This Patient Information has been approved by the U.S. Food and Drug Administration.

Revised: 10/2022

Representative sample of labeling (see the HOW SUPPLIED section for complete listing):

PRINCIPAL DISPLAY PANEL - 63 Tablet Bottle Label

NDC 50242-717-01

Cotellic®
(cobimetinib)
tablets

20 mg

Rx only

63 tablets
Genentech

10176377